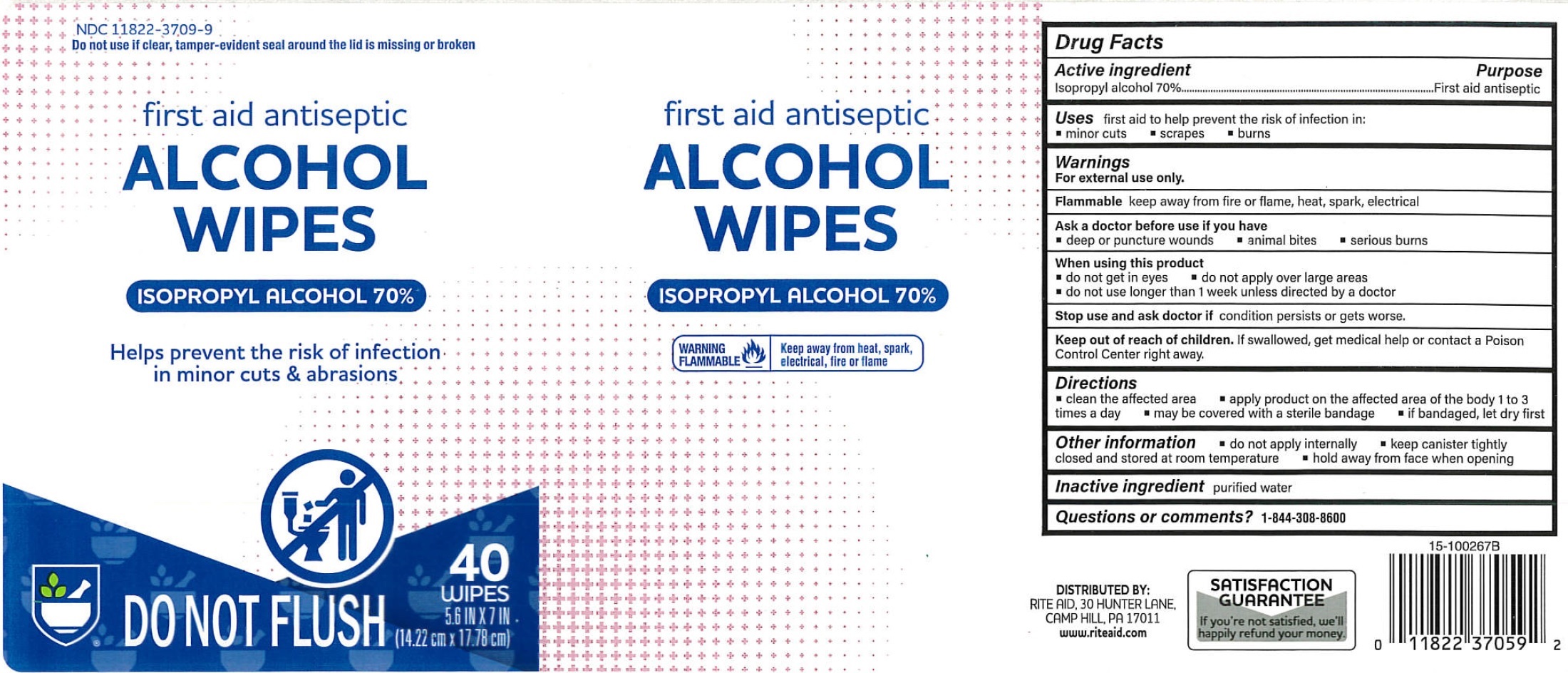 DRUG LABEL: Rite Aid Isopropyl Alcohol Wipes
NDC: 11822-3709 | Form: CLOTH
Manufacturer: Rite Aid
Category: otc | Type: HUMAN OTC DRUG LABEL
Date: 20260122

ACTIVE INGREDIENTS: ISOPROPYL ALCOHOL 70 mL/100 mL
INACTIVE INGREDIENTS: WATER

Rite Aid Isopropyl Alcohol Wipes

Active ingredient

Isopropyl alcohol 70%

Purpose

First aid antiseptic

Uses

first aid to help prevent the risk of infection in:

- minor cuts
- scrapes
- burns

Warnings

For external use only.

keep away from fire or flame, heat, spark, electrical Flammable

Ask a doctor before use if you have

- deep or puncture wounds
- animal bites
- serious burns

When using this product

- do not get in eyes
- do not apply over large areas
- do not use longer than 1 week unless directed by a doctor

Stop use and ask doctor if

condition persists or gets worse.

Keep out of reach of children.

If swallowed, get medical help or contact a Poison Control Center right away.

Directions

- clean the affected area
- apply product on the affected area of the body 1 to 3 times a day
- may by covered with a sterile bandage
- if bandaged, let dry frist

Other information

- do not apply internally
- keep canister tightly closed and stored at room temperature
- hold away from face when opening

Inactive ingredient

purified water

Questions or comments?

1-844-308-8600